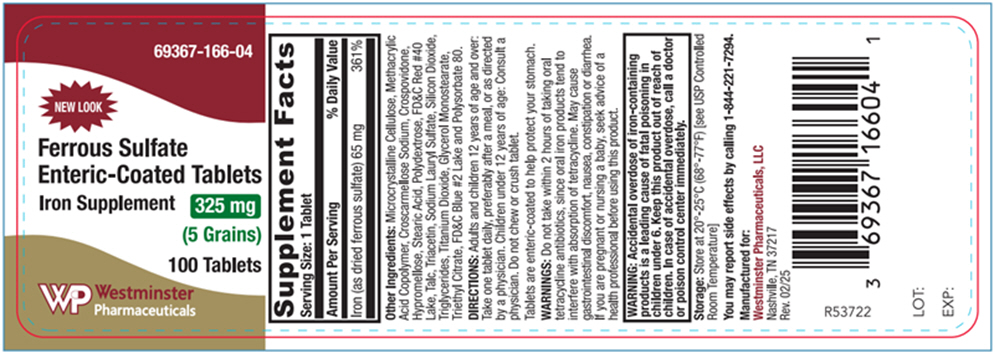 DRUG LABEL: Ferrous Sulfate
NDC: 69367-166 | Form: TABLET, COATED
Manufacturer: Westminster Pharmaceuticals, LLC
Category: other | Type: DIETARY SUPPLEMENT
Date: 20250707

ACTIVE INGREDIENTS: FERROUS SULFATE 65 mg/1 1
INACTIVE INGREDIENTS: CALCIUM CARBONATE; HYPROMELLOSE, UNSPECIFIED; CROSCARMELLOSE SODIUM; COPOVIDONE K25-31; POLYDEXTROSE; TALC; TRIACETIN; SODIUM LAURYL SULFATE; MEDIUM-CHAIN TRIGLYCERIDES; GLYCERYL MONOSTEARATE; TRIETHYL CITRATE; FD&C BLUE NO. 2 ALUMINUM LAKE; POLYSORBATE 80

FERROUS SULFATE ENTERIC COATED

STATEMENT OF IDENTITY

Supplement Facts
Serving Size: 1 Tablet
Amount Per Serving | % Daily Value
Iron (as dried ferrous sulfate) 65 mg | 361%

Other Ingredients: Microcrystalline Cellulose, Methacrylic Acid Copolymer, Croscarmellose Sodium, Crospovidone, Hypromellose, Stearic Acid, Polydextrose, FD&C Red #40 Lake, Talc, Triacetin, Sodium Lauryl Sulfate, Silicon Dioxide, Triglycerides, Titanium Dioxide, Glycerol Monostearate, Triethyl Citrate, FD&C Blue #2 Lake and Polysorbate 80.

DIRECTIONS

Adults and children 12 years of age and over: Take one tablet daily, preferably after a meal, or as directed by a physician. Children under 12 years of age: Consult a physician. Do not chew or crush tablet.

Tablets are enteric-coated to help protect your stomach.

WARNINGS

Do not take within 2 hours of taking oral tetracycline antibiotics, since oral iron products tend to interfere with absorption of tetracycline. May cause gastrointestinal discomfort, nausea, constipation or diarrhea. If you are pregnant or nursing a baby, seek advice of a health professional before using this product.

SAFE HANDLING WARNING

WARNING: Accidental overdose of iron-containing products is a leading cause of fatal poisoning in children under 6. Keep this product out of reach of children. In case of accidental overdose, call a doctor or poison control center immediately.

Storage

Store at 20°-25°C (68°-77°F) [see USP Controlled Room Temperature]

HEALTH CLAIM

You may report side effects by calling 1-844-221-7294.

HEALTH CLAIM

Manufactured for:
Westminster Pharmaceuticals, LLC
Nashville, TN 37217

Rev. 02/25

R53722

LOT:
EXP:

PRINCIPAL DISPLAY PANEL - 325 mg Tablet Bottle Label

NEW LOOK

69367-166-04

Ferrous Sulfate
Enteric-Coated Tablets

Iron Supplement

325 mg

(5 Grains)

100 Tablets

Westminster
Pharmaceuticals